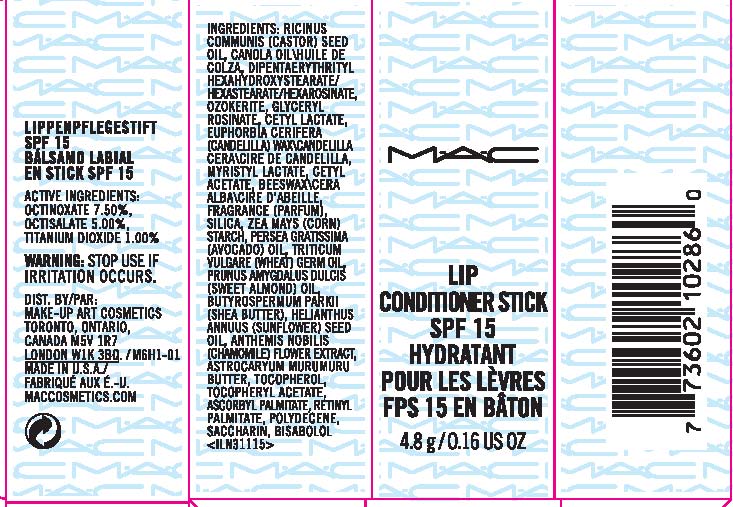 DRUG LABEL: LIP CONDITIONER
NDC: 40046-0053 | Form: LIPSTICK
Manufacturer: MAKE UP ART COSMETICS
Category: otc | Type: HUMAN OTC DRUG LABEL
Date: 20111026

ACTIVE INGREDIENTS: OCTINOXATE 7.5 g/100 g; OCTISALATE 5.0 g/100 g; TITANIUM DIOXIDE 1.0 g/100 g
INACTIVE INGREDIENTS: CASTOR OIL; CERESIN; CANDELILLA WAX; MYRISTYL LACTATE; YELLOW WAX; SILICON DIOXIDE; STARCH, CORN; AVOCADO OIL; WHEAT GERM OIL; ALMOND OIL; SHEA BUTTER; SUNFLOWER OIL; CHAMAEMELUM NOBILE FLOWER; ASTROCARYUM MURUMURU SEED BUTTER; ALPHA-TOCOPHEROL; ALPHA-TOCOPHEROL ACETATE; ASCORBYL PALMITATE; VITAMIN A PALMITATE; SACCHARIN; LEVOMENOL

ACTIVE INGREDIENT

ACTIVE INGREDIENTS: OCTINOXATE 7.50% [] OCTISALATE 5.00% [] TITANIUM DIOXIDE 1.00%

INACTIVE INGREDIENT

INGREDIENTS: RICINUS COMMUNIS (CASTOR) SEED OIL [] CANOLA OIL\HUILE DE COLZA [] DIPENTAERYTHRITYL HEXAHYDROXYSTEARATE/HEXASTEARATE/HEXAROSINATE [] OZOKERITE [] GLYCERYL ROSINATE [] CETYL LACTATE [] EUPHORBIA CERIFERA (CANDELILLA) WAX\CANDELILLA CERA\CIRE DE CANDELILLA [] MYRISTYL LACTATE [] CETYL ACETATE [] BEESWAX\CERA ALBA\CIRE D’ABEILLE [] FRAGRANCE (PARFUM) [] SILICA [] ZEA MAYS (CORN) STARCH [] PERSEA GRATISSIMA (AVOCADO) OIL [] TRITICUM VULGARE (WHEAT) GERM OIL [] PRUNUS AMYGDALUS DULCIS (SWEET ALMOND) OIL [] BUTYROSPERMUM PARKII (SHEA BUTTER) [] HELIANTHUS ANNUUS (SUNFLOWER) SEED OIL [] ANTHEMIS NOBILIS (CHAMOMILE) FLOWER EXTRACT [] ASTROCARYUM MURUMURU BUTTER [] TOCOPHEROL [] TOCOPHERYL ACETATE [] ASCORBYL PALMITATE [] RETINYL PALMITATE [] POLYDECENE [] SACCHARIN [] BISABOLOL

WARNINGS

WARNINGS: KEEP OUT OF EYES. STOP USE IF IRRITATION OCCURS. KEEP OUT OF REACH OF CHILDREN.

PACKAGE LABEL

PRINCIPAL DISPLAY PANEL:

MAC

LIP CONDITIONER STICK

SPF 15

4.8 g/0.16 oz

distr make up art cosmetics

Toronto, Ontario

Canada m5v 1r7